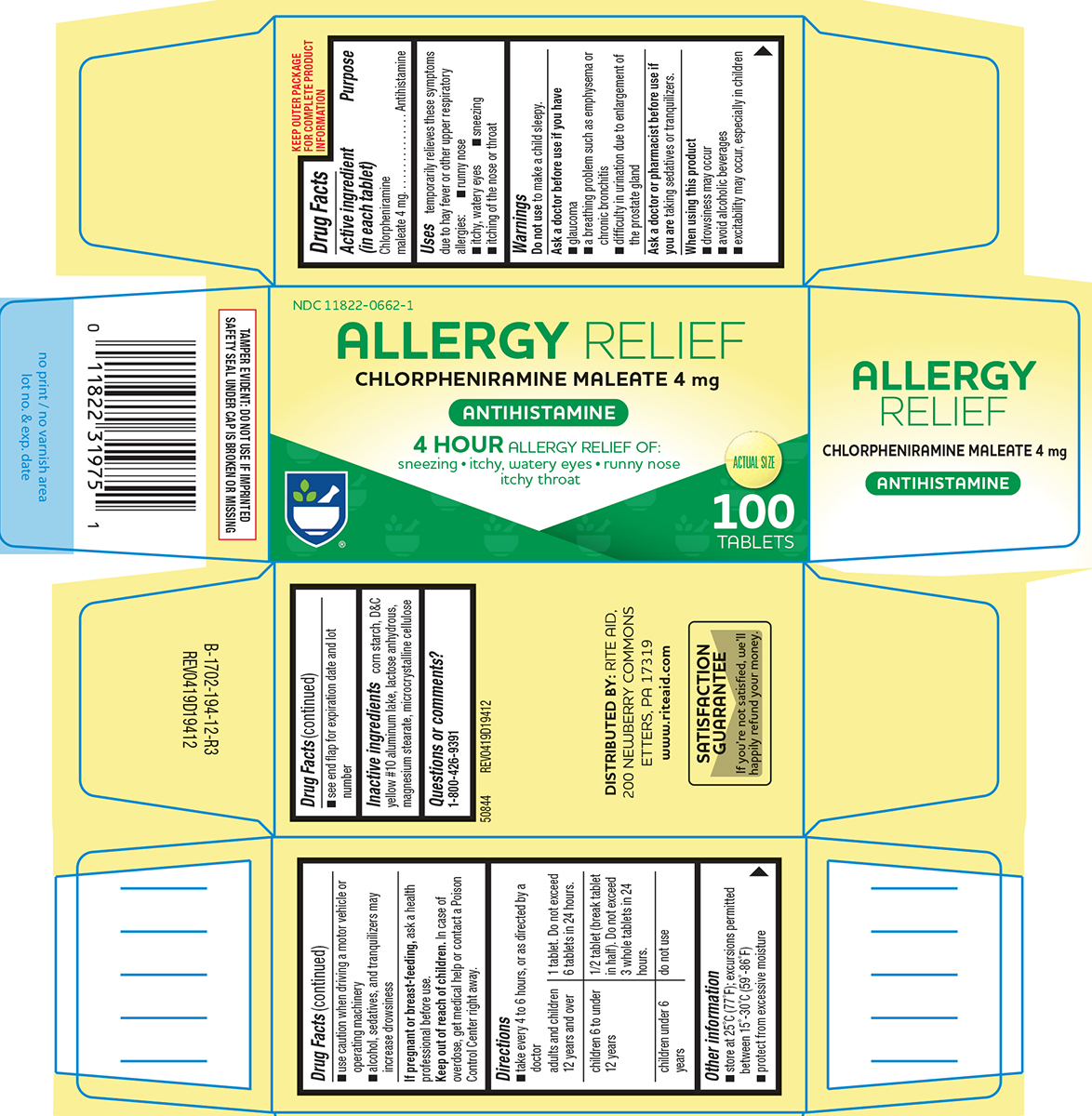 DRUG LABEL: allergy relief
NDC: 11822-0662 | Form: TABLET
Manufacturer: Rite Aid Corporation
Category: otc | Type: HUMAN OTC DRUG LABEL
Date: 20260218

ACTIVE INGREDIENTS: CHLORPHENIRAMINE MALEATE 4 mg/1 1
INACTIVE INGREDIENTS: STARCH, CORN; D&C YELLOW NO. 10 ALUMINUM LAKE; ANHYDROUS LACTOSE; MAGNESIUM STEARATE; MICROCRYSTALLINE CELLULOSE

Rite Aid 44-194

Active ingredient (in each tablet)

Chlorpheniramine maleate 4 mg

Purpose

Antihistamine

Uses

temporarily relieves these symptoms due to hay fever or other upper respiratory allergies:

- runny nose
- itchy, watery eyes
- sneezing
- itching of the nose or throat

Warnings

Do not use

to make a child sleepy.

Ask a doctor before use if you have

- glaucoma
- a breathing problem such as emphysema or chronic bronchitis
- difficulty in urination due to enlargement of the prostate gland

Ask a doctor or pharmacist before use if you are

taking sedatives or tranquilizers.

When using this product

- drowsiness may occur
- avoid alcoholic beverages
- excitability may occur, especially in children
- use caution when driving a motor vehicle or operating machinery
- alcohol, sedatives, and tranquilizers may increase drowsiness

If pregnant or breast-feeding,

ask a health professional before use.

Keep out of reach of children.

In case of overdose, get medical help or contact a Poison Control Center right away.

Directions

- take every 4 to 6 hours, or as directed by a doctor

adults and children 12 years and over | 1 tablet. Do not exceed 6 tablets in 24 hours.
children 6 to under 12 years | 1/2 tablet (break tablet in half). Do not exceed 3 whole tablets in 24 hours.
children under 6 years | do not use

Other information

- store at 25°C (77°F); excursions permitted between 15°-30°C (59°-86°F)
- protect from excessive moisture
- see end flap for expiration date and lot number

Inactive ingredients

corn starch, D&C yellow #10 aluminum lake, lactose anhydrous, magnesium stearate, microcrystalline cellulose

Questions or comments?

1-800-426-9391

Principal Display Panel

NDC 11822-0662-1

ALLERGY RELIEF
CHLORPHENIRAMINE MALEATE 4 mg

ANTIHISTAMINE

4 HOUR ALLERGY RELIEF OF:
sneezing • itchy, watery eyes • runny nose
itchy throat

ACTUAL SIZE

100
TABLETS

TAMPER EVIDENT: DO NOT USE IF IMPRINTED
SAFETY SEAL UNDER CAP IS BROKEN OR MISSING

50844 REV0419D19412

DISTRIBUTED BY: RITE AID,
200 NEWBERRY COMMONS
ETTERS, PA 17319
www.riteaid.com

SATISFACTION
GUARANTEE
If you’re not satisfied, we’ll
happily refund your money.

Rite Aid 44-194